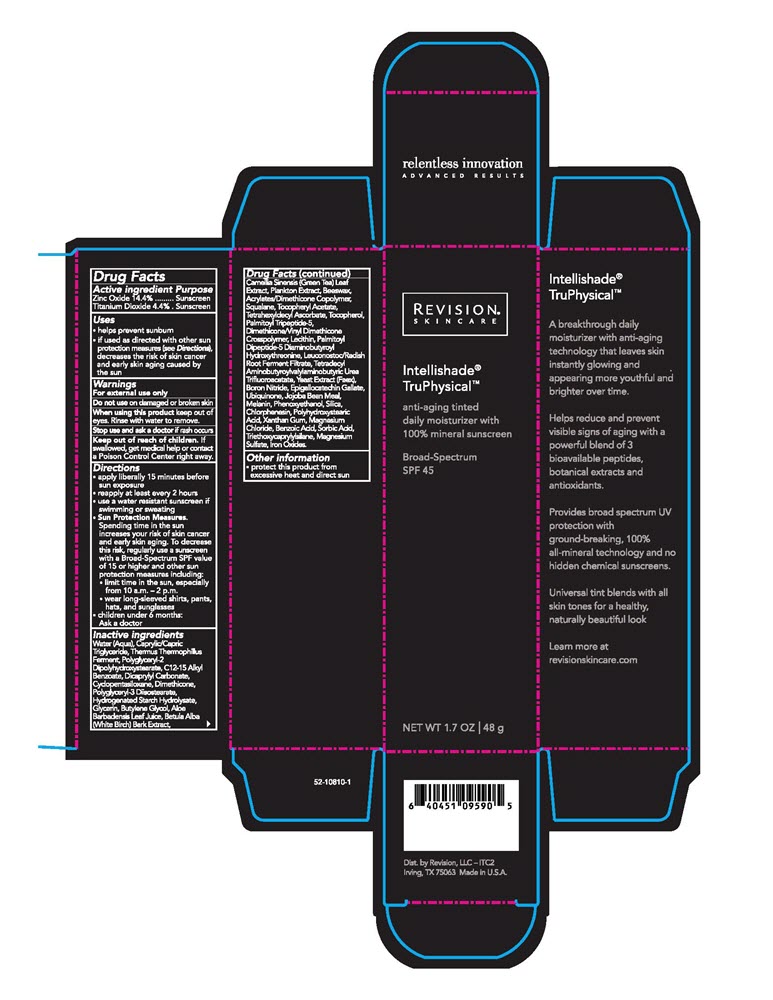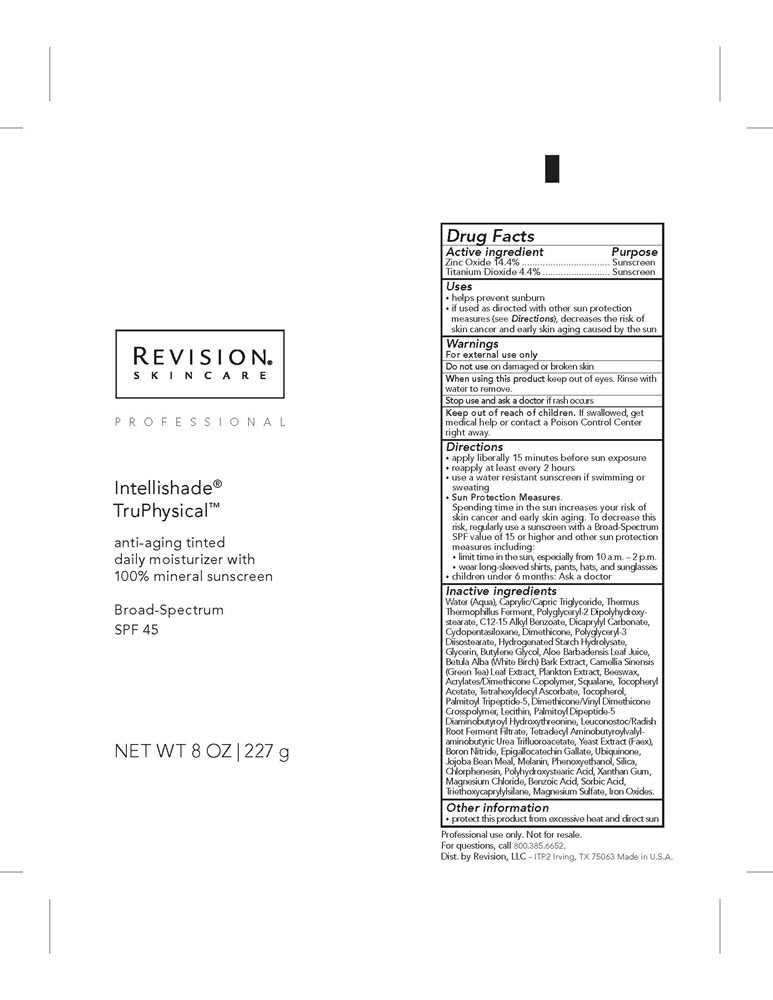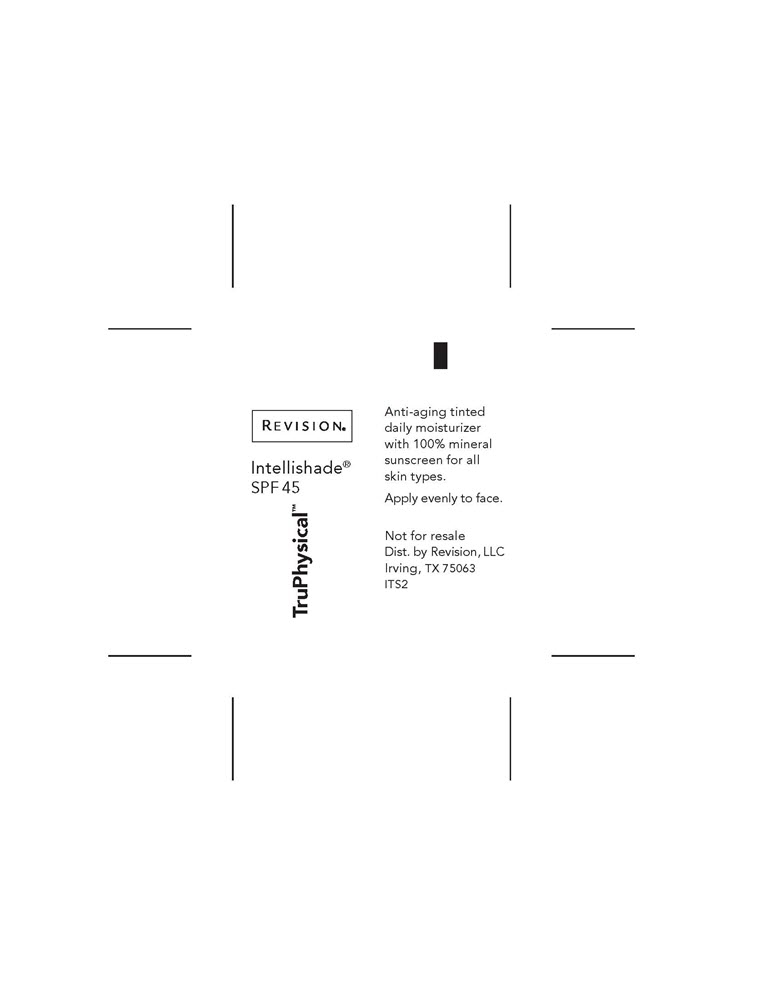 DRUG LABEL: All Physical Sunscreen Broad Spectrum SPF 50
NDC: 10477-1003 | Form: LOTION
Manufacturer: Goodier Cosmetics LLC
Category: otc | Type: HUMAN OTC DRUG LABEL
Date: 20211015

ACTIVE INGREDIENTS: TITANIUM DIOXIDE 4.4 g/100 g; ZINC OXIDE 14.4 g/100 g
INACTIVE INGREDIENTS: WATER; MEDIUM-CHAIN TRIGLYCERIDES; THERMUS THERMOPHILUS; POLYGLYCERYL-2 DIPOLYHYDROXYSTEARATE; ALKYL (C12-15) BENZOATE; DICAPRYLYL CARBONATE; CYCLOMETHICONE 5; DIMETHICONE; POLYGLYCERYL-3 DIISOSTEARATE; SORBITOL; GLYCERIN; BUTYLENE GLYCOL; ALOE VERA LEAF; WHITE WAX; SQUALANE; .ALPHA.-TOCOPHEROL ACETATE, DL-; TETRAHEXYLDECYL ASCORBATE; .ALPHA.-TOCOPHEROL; PALMITOYL TRIPEPTIDE-5; DIMETHICONE/VINYL DIMETHICONE CROSSPOLYMER (SOFT PARTICLE); LECITHIN, SOYBEAN; PALMITOYLLYSYLVALYLDIAMINOBUTYROYLTHREONINE; LEUCONOSTOC/RADISH ROOT FERMENT FILTRATE; YEAST, UNSPECIFIED; BORON NITRIDE; EPIGALLOCATECHIN GALLATE; UBIQUINONE Q2; MELANIN SYNTHETIC (TYROSINE, PEROXIDE); PHENOXYETHANOL; SILICON DIOXIDE; CHLORPHENESIN; POLYHYDROXYSTEARIC ACID (2300 MW); XANTHAN GUM; MAGNESIUM CHLORIDE; BENZOIC ACID; SORBIC ACID; TRIETHOXYCAPRYLYLSILANE; MAGNESIUM SULFATE HEPTAHYDRATE

All Physical Sunscreen

Intellishade®
TruPhysical™

anti-aging tinted
daily moisturizer with
100% mineral sunscreen

Broad-Spectrum
SPF 45

Intellishade®
TruPhysical™

A breakthrough daily moisturizer with anti-aging technology that leaves skin instantly glowing and
appearing more youthful and brighter over time.

Helps reduce and prevent visible signs of aging with a powerful blend of 3 bioavailable peptides,
botanical extracts and antioxidants.

Provides broad spectrum UV protection with ground-breaking,
100% all-mineral technology and no hidden chemical sunscreens.

Universal tint blends with all skin tones for a healthy, naturally beautiful look.

Dist. by Revision, LLC – ITC1
Irving, TX 75063 Made in U.S.A.

Active ingredient Purpose
Zinc Oxide 14.4% ......... Sunscreen
Titanium Dioxide 4.4% . Sunscreen

Uses
• helps prevent sunburn
• if used as directed with other sun protection measures (see Directions),
decreases the risk of skin cancer and early skin aging caused by the sun

Warnings
For external use only

Do not use on damaged or broken skin

When using this product keep out of eyes. Rinse with water to remove.

Stop use and ask a doctor if rash occurs

Keep out of reach of children. If swallowed, get medical help or contact
a Poison Control Center right away.

Directions
• apply liberally 15 minutes before sun exposure
• reapply at least every 2 hours
• use a water resistant sunscreen if swimming or sweating
• Sun Protection Measures.
Spending time in the sun increases your risk of skin cancer and early skin aging.
To decrease this risk, regularly use a sunscreen with a Broad-Spectrum SPF value
of 15 or higher and other sun protection measures including:
• limit time in the sun, especially from 10 a.m. – 2 p.m.
• wear long-sleeved shirts, pants, hats, and sunglasses
• children under 6 months: Ask a doctor

Inactive ingredients
Water (Aqua), Caprylic/Capric Triglyceride, Thermus Thermophillus Ferment,
Polyglyceryl-2 Dipolyhydroxystearate, C12-15 Alkyl Benzoate, Dicaprylyl Carbonate,
Cyclopentasiloxane, Dimethicone, Polyglyceryl-3 Diisostearate, Hydrogenated
Starch Hydrolysate, Glycerin, Butylene Glycol, Aloe Barbadensis Leaf Juice, Betula
Alba (White Birch) Bark Extract, Camellia Sinensis (Green Tea) Leaf Extract, Plankton
Extract, Beeswax, Acrylates/Dimethicone Copolymer, Squalane, Tocopheryl Acetate,
Tetrahexyldecyl Ascorbate, Tocopherol, Palmitoyl Tripeptide-5, Dimethicone/Vinyl
Dimethicone Crosspolymer, Lecithin, Palmitoyl Dipeptide-5 Diaminobutyroyl
Hydroxythreonine, Leuconostoc/Radish Root Ferment Filtrate, Tetradecyl
Aminobutyroylvalylaminobutyric Urea Tri-uoroacetate, Yeast Extract (Faex), Boron
Nitride, Epigallocatechin Gallate, Ubiquinone, Jojoba Bean Meal, Melanin, Phenoxyethanol,
Silica, Chlorphenesin, Polyhydroxystearic Acid, Xanthan Gum, Magnesium Chloride,
Benzoic Acid, Sorbic Acid, Triethoxycaprylylsilane, Magnesium Sulfate, Iron Oxides.

Other information
• protect this product from excessive heat and direct sun

PACKAGE LABEL

1.7oz Intellishade® TruPhysical™

8oz Intellishade® TruPhysical™

3gm Sampler Intellishade® TruPhysical™